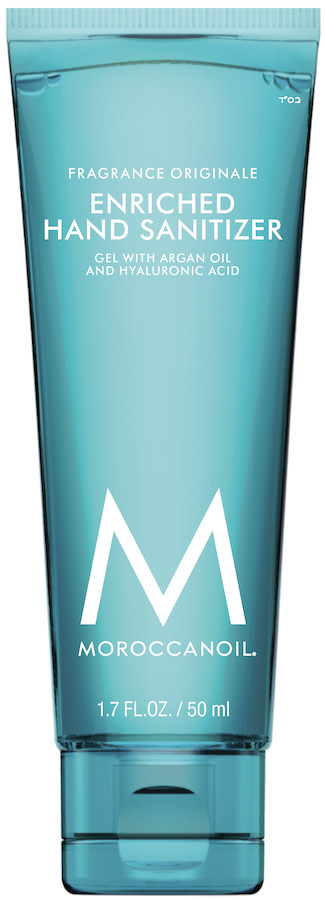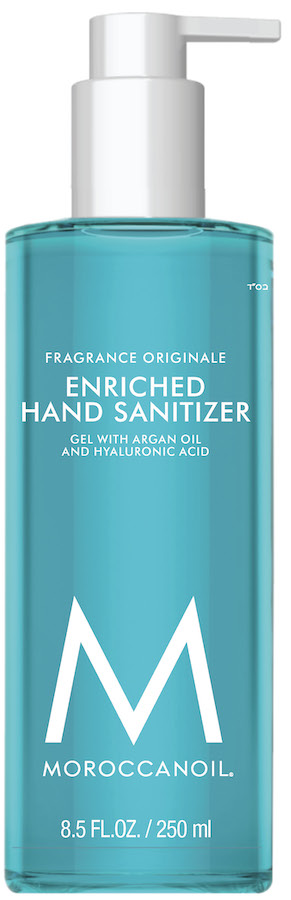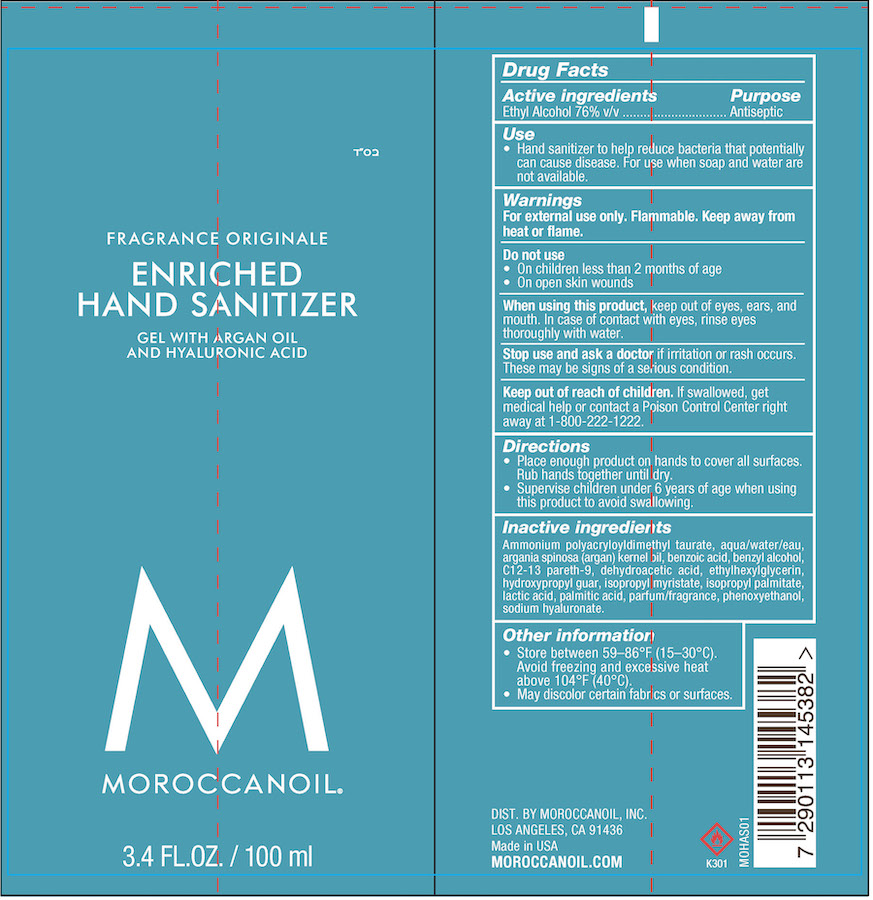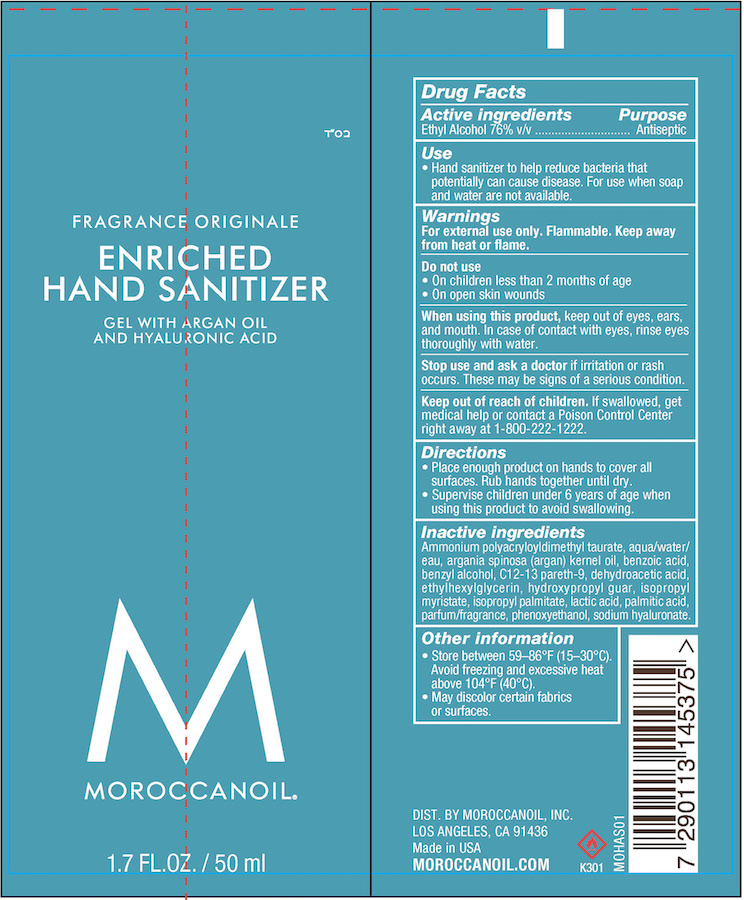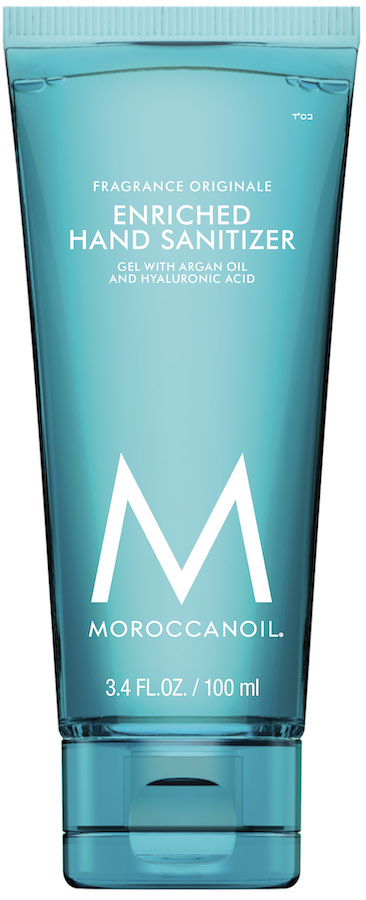 DRUG LABEL: Hand Sanitizer
NDC: 69942-010 | Form: GEL
Manufacturer: Moroccanoil
Category: otc | Type: HUMAN OTC DRUG LABEL
Date: 20221213

ACTIVE INGREDIENTS: ALCOHOL 76 mL/100 mL
INACTIVE INGREDIENTS: BENZYL ALCOHOL; LACTIC ACID; C12-13 PARETH-9; ETHYLHEXYLGLYCERIN; ISOPROPYL PALMITATE; PALMITIC ACID; PEG-9 DIGLYCIDYL ETHER/SODIUM HYALURONATE CROSSPOLYMER; PHENOXYETHANOL; ISOPROPYL MYRISTATE; HYDROXYPROPYL GUAR (2500-4500 MPA.S AT 1%); ARGANIA SPINOSA SEED; DEHYDROACETIC ACID; WATER; BENZOIC ACID

Active Ingredient(s)

Ethyl Alcohol 76% v/v. Purpose: Antiseptic

Purpose

Antiseptic

Use

Hand Sanitizer to help reduce bacteria that potentially can cause disease. For use when soap and water are not available.

Warnings

For external use only. Flammable. Keep away from heat or flame

Do not use

- in children less than 2 months of age
- on open skin wounds

When using this product keep out of eyes, ears, and mouth. In case of contact with eyes, rinse eyes thoroughly with water.
Stop use and ask a doctor if irritation or rash occurs. These may be signs of a serious condition.
Keep out of reach of children. If swallowed, get medical help or contact a Poison Control Center right away.

Stop use and ask a doctor if irritation or rash occurs. These may be signs of a serious condition.

Keep out of reach of children. If swallowed, get medical help or contact a Poison Control Center right away.

Directions

- Place enough product on hands to cover all surfaces. Rub hands together until dry.
- Supervise children under 6 years of age when using this product to avoid swallowing.

Other information

- Store between 15-30C (59-86F)
- Avoid freezing and excessive heat above 40C (104F)

Inactive ingredients

Ammonium polyacryloyldimethyl taurate, aqua/water/eau, argania spinosa (argan) kernel oil, benzoic acid, benzyl alcohol, C12-13 pareth-9, dehydroacetic acid, ethylhexylglycerin, hydroxypropyl guar, isopropyl myristate, isopropyl palmitate, lactic acid, palmitic acid, parfum/fragrance, phenoxyethanol, sodium hyaluronate.

Package Label - Principal Display Panel

50 ml NDC: 69942-010-05

100 ml NDC: 69942-010-10

250 ml NDC: 69942-010-25